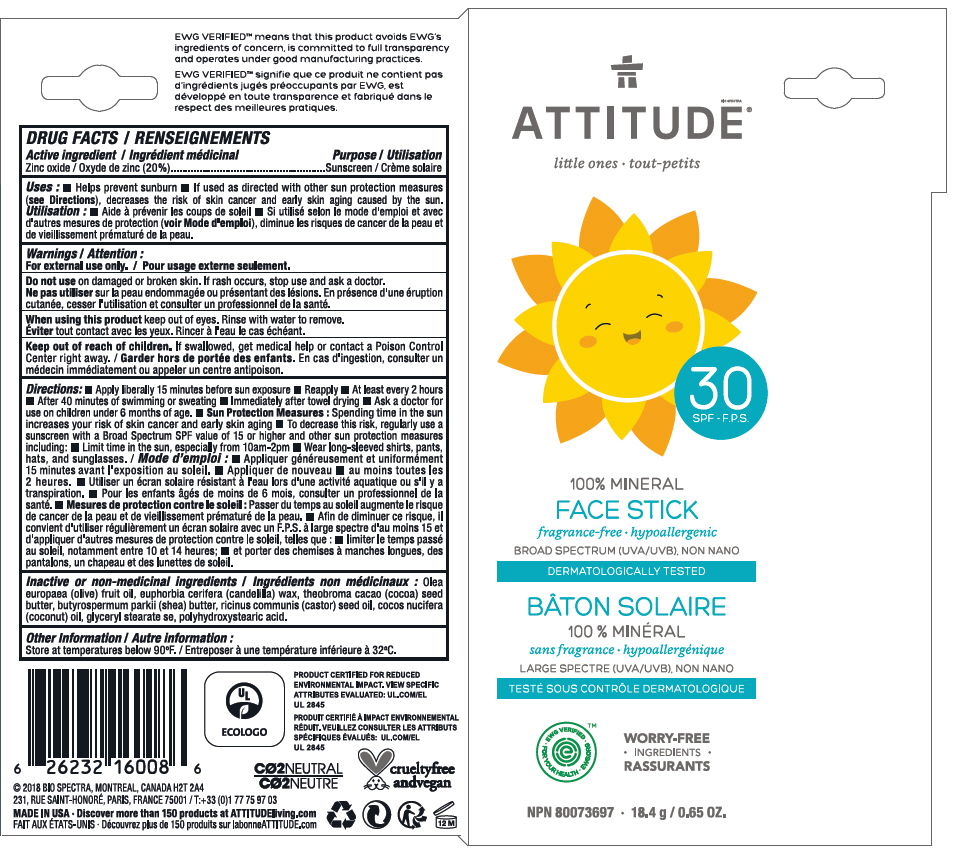 DRUG LABEL: ATTITUDE 
NDC: 61649-013 | Form: STICK
Manufacturer: Bio Spectra
Category: otc | Type: HUMAN OTC DRUG LABEL
Date: 20180706

ACTIVE INGREDIENTS: ZINC OXIDE 20 g/100 g
INACTIVE INGREDIENTS: OLIVE OIL; CANDELILLA WAX; COCOA BUTTER; SHEA BUTTER; CASTOR OIL; COCONUT OIL; GLYCERYL STEARATE SE; POLYHYDROXYSTEARIC ACID (2300 MW)

ATTITUDE®
Mineral Face SPF30 - Little Ones

DRUG FACTS

Active ingredient

Zinc oxide (20%)

Purpose

Sunscreen

Uses

- Helps prevent sunburn
- If used as directed with other sun protection measures (see Directions), decreases the risk of skin cancer and early skin aging caused by the sun.

Warnings

For external use only.

Do not use on damaged or broken skin. If rash occurs, discontinue use.

When using this product keep out of eyes. Rinse with water to remove.

Keep out of reach of children. If swallowed, get medical help or contact a Poison Control Center right away

DIRECTIONS

- Apply liberally 15 minutes before sun exposure
- Reapply:
  - At least every 2 hours
  - After 40 minutes of swimming or sweating
  - Immediately after towel drying
- Ask a doctor for use on children under 6 months of age.
- Sun Protection Measures: Spending time in the sun increases your risk of skin cancer and early skin aging
  - To decrease this risk, regularly use a sunscreen with a Broad Spectrum SPF value of 15 or higher and other sun protection measures including:
    - Limit time in the sun, especially from 10am–2pm
    - Wear long-sleeved shirts, pants, hats, and sunglasses.

Inactive or non-medicinal ingredients

Olea europaea (olive) fruit oil, euphorbia cerifera (candelilla) wax, theobroma cacao (cocoa) seed butter, butyrospermum parkii (shea) butter, ricinus communis (castor) seed oil, cocos nucifera (coconut) oil, glyceryl stearate se, polyhydroxystearic acid.

Other Information

Store at temperatures below 90°F.

PRINCIPAL DISPLAY PANEL - 18.4 g Tube Carton

BIO SPECTRA
ATTITUDE®

little ones

30
SPF

100% MINERAL
FACE STICK

fragrance-free • hypoallergenic

BROAD SPECTRUM (UVA/UVB), NON NANO

DERMATOLOGICALLY TESTED

• EWG VERIFIED
FOR YOUR HEALTH •
EWG.ORG •™

WORRY-FREE
• INGREDIENTS •

NPN 80073697 • 18.4 g / 0.65 OZ.